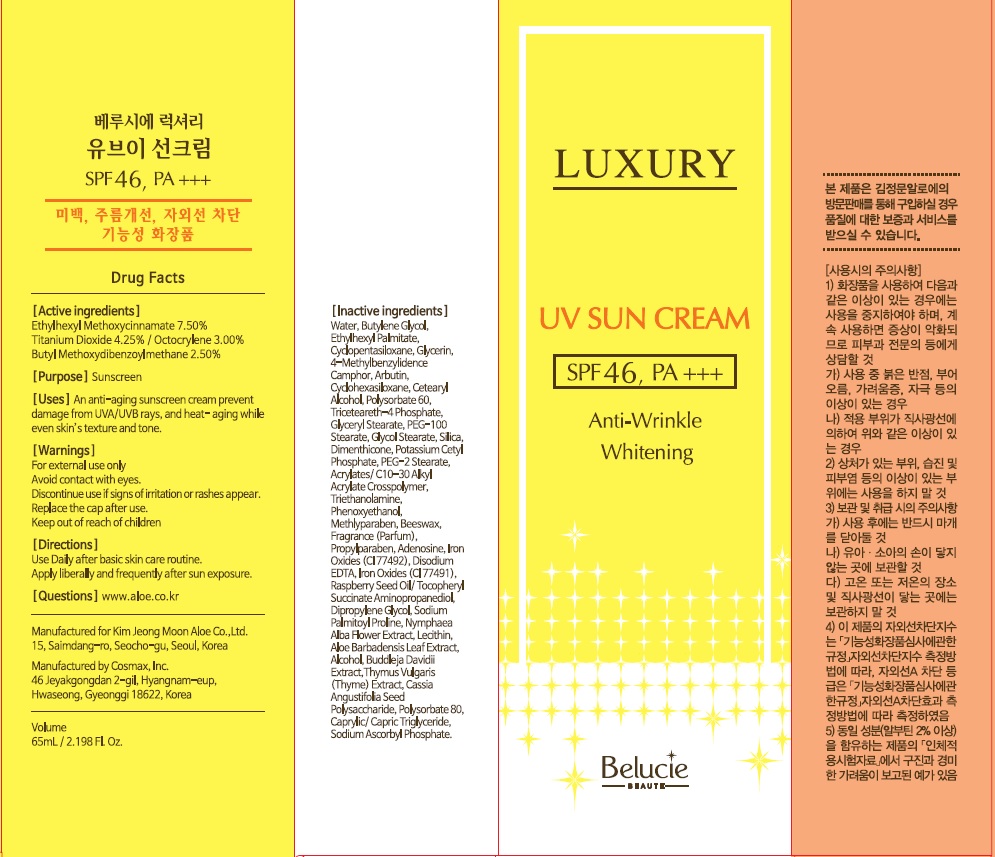 DRUG LABEL: Belucie Luxury UV Sun
NDC: 50410-110 | Form: CREAM
Manufacturer: Kimjeongmoon Aloe Co., Ltd.
Category: otc | Type: HUMAN OTC DRUG LABEL
Date: 20181122

ACTIVE INGREDIENTS: Octinoxate 4.87 g/65 mL; Titanium Dioxide 2.76 g/65 mL; Octocrylene 1.95 g/65 mL; Avobenzone 1.62 g/65 mL
INACTIVE INGREDIENTS: Water; Butylene Glycol

ACTIVE INGREDIENT

Active ingredients: Ethylhexyl Methoxycinnamate 7.50%, Titanium2. Dioxide 4.25%, Octocrylene 3.00%, Butyl Methoxydibenzoylmethane 2.50%

INACTIVE INGREDIENT

Inactive ingredients:

Water, Butylene Glycol, Ethylhexyl Palmitate, Cyclopentasiloxane, Glycerin, 4-Methylbenzylidence Camphor, Arbutin, Cyclohexasiloxane, Cetearyl Alcohol, Polysorbate 60, Triceteareth-4 Phosphate, Glyceryl Stearate, PEG-100 Stearate, Glycol Stearate, Silica, Dimenthicone, Potassium Cetyl Phosphate, PEG-2 Stearate, Acrylates/ C10-30 Alkyl Acrylate Crosspolymer, Triethanolamine, Phenoxyethanol, Methlyparaben, Beeswax, Fragrance (Parfum), Propylparaben, Adenosine, Iron Oxides (CI 77492), Disodium EDTA, Iron Oxides (CI 77491), Raspberry Seed Oil/ Tocopheryl Succinate Aminopropanediol, Dipropylene Glycol, Sodium Palmitoyl Proline, Nymphaea Alba Flower Extract, Lecithin, Aloe Barbadensis Leaf Extract, Alcohol, Buddleja Davidii Extract,Thymus Vulgaris (Thyme) Extract, Cassia Angustifolia Seed Polysaccharide, Polysorbate 80, Caprylic/ Capric Triglyceride, Sodium Ascorbyl Phosphate.

PURPOSE

Purpose: Sunscreen

WARNINGS

For external use only

Avoid contact with eyes.

Discontinue use if signs of irritation or rashes appear.

Replace the cap after use.

Keep out of reach of children

DESCRIPTION

Uses:

An anti-aging sunscreen cream prevent damage from UVA/UVB rays, and heat- aging while even skin’s texture and tone.

Directions:

Use Daily after basic skin care routine.

Apply liberally and frequently after sun exposure.